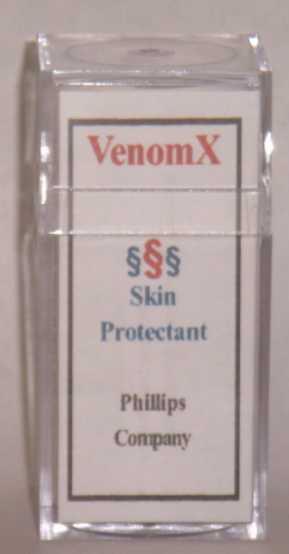 DRUG LABEL: VenomX
NDC: 43074-207 | Form: LIQUID
Manufacturer: Phillips Company
Category: otc | Type: HUMAN OTC DRUG LABEL
Date: 20100904

ACTIVE INGREDIENTS: zinc acetate 0.001 mg/1 mL
INACTIVE INGREDIENTS: dimethyl sulfoxide; ascorbic acid; dipropylene glycol; water; glycerin; chlorhexidine gluconate; calcium gluconate; methylparaben; sodium hydroxide; sorbic acid; magnesium stearate; stearic acid; witch hazel; sodium dodecylbenzenesulfonate

DRUG FACTS

DRUG FACTS

Questions and Side effects
Use of this product results in no known side effects when used according to directions. Phillips Company, 311 Chickasaw Street, Millerton, OK USA 74750; Tel. 580-746-2430
Email address: hp@valliant.net

ACTIVE INGREDIENTS

Active Ingredients Purpose
Zinc acetate (.1% by volume) Skin Protectant

ASK DOCTOR

Ask a doctor
If symptoms last for more than 7 days or clear up and recur within a few days.
If the conditions do not improve.
Before use on children under 2 years.
Before use if you are allergic to any ingredients listed on this label.

DO NOT USE

Warnings
For external use only
Keep away from children
Avoid contact with eyes
May be harmful if swallowed or inhaled

CHILDREN

Keep away from children
Avoid contact with eyes
May be harmful if swallowed or inhaled

PURPOSE

Active Ingredients Purpose
Zinc acetate (.1% by volume) Skin Protectant

STOP USE

If symptoms last for more than 7 days or clear up and recur within a few days.
If the conditions do not improve.
Before use on children under 2 years.
Before use if you are allergic to any ingredients listed on this label.

WHEN USING

For external use only
Avoid contact with eyes
May be harmful if swallowed or inhaled
If symptoms last for more than 7 days or clear up and recur within a few days.
If the conditions do not improve.
Store at 40 to 120 degrees F.

WARNINGS

For external use only
Keep away from children
Avoid contact with eyes
May be harmful if swallowed or inhaled
Use of this product results in no known side effects when used according to directions.

Phillips Company, 311 Chickasaw Street, Millerton, OK USA 74750; Tel. 580-746-2430
Email address: hp@valliant.net

DOSAGE & ADMINISTRATION

Uses
Temporarily protects injured or exposed skin or mucous membrane surfaces from harmful or annoying stimuli and may help provide relief to such surfaces
Directions
Apply to affected skin area and rub gently. Repeat the process as needed.

USE

Uses
Temporarily protects injured or exposed skin or mucous membrane surfaces from harmful or annoying stimuli and may help provide relief to such surfaces
Apply to affected skin area and rub gently. Repeat the process as needed.

INACTIVE INGREDIENTS

Water, color, glycerin, hydroxethylcellulose, chlor-hexidine gluconate, glucono delta lactone, methylparaben, sodium hydroxide,sodium dodecylbenzene sulfonate, dimethyl sulfoxide, witch hazel, ascorbic acid, magnesium stearate, silica and stearic acid.

Image of product